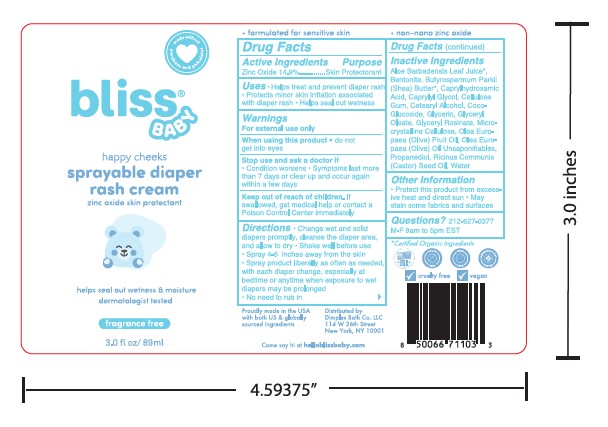 DRUG LABEL: Diaper Rash Cream Happy Cheeks
NDC: 84568-549 | Form: CREAM
Manufacturer: Dimples Bath Co. LLC
Category: otc | Type: HUMAN OTC DRUG LABEL
Date: 20250106

ACTIVE INGREDIENTS: ZINC OXIDE 14.9 g/100 mL
INACTIVE INGREDIENTS: GLYCERYL OLEATE; WATER; BUTYROSPERMUM PARKII (SHEA) BUTTER; GLYCERIN; MICROCRYSTALLINE CELLULOSE; OLEA EUROPAEA (OLIVE) FRUIT OIL; CELLULOSE GUM; CETEARYL ALCOHOL; RICINUS COMMUNIS (CASTOR) SEED OIL; PROPANEDIOL; BENTONITE; CAPRYLHYDROXAMIC ACID; COCO-GLUCOSIDE; GLYCERYL ROSINATE; OLEA EUROPAEA (OLIVE) OIL UNSAPONIFIABLES; ALOE BARBADENSIS LEAF JUICE; CAPRYLYL GLYCOL

Diaper Rash Cream Happy Cheeks 02-AP-123

ACTIVE INGREDIENT

Zinc Oxide 14.9%

PURPOSE

Skin Protectorant

Uses

Helps treat and prevent diaper rash. Protects minor skin irritation associated with diaper rash. Helps seal out wetness

WARNINGS

For external use only

When using this product • do not get into eyes

Stop use and ask a doctor if

• Condition worsens • Symptoms last more than 7 days or clear up and occur again within a few days

KEEP OUT OF REACH OF CHILDREN

If swallowed, get medical help or contact a Poison Control Center immediately

DOSAGE AND ADMINISTRATION

Change wet and soild diapers promptly, cleanse the diaper area, and allow to dry. Shake well before use. Spray 4-6 inches away from the skin. Spray product liberally as often as needed, with each diaper change, especially at bedtime or anytime when exposure to wet diapers may be prolonged. No need to rub in

INACTIVE INGREDIENT

Aloe Barbadensis Leaf Juice, Bentonite, Butyrospermum Parkii (Shea) Butter, Caprylhydroxamic Acid, Caprylyl Glycol, Cellulose Gum, Cetearyl Alcohol, Coco Glucoside, Glycerin, Glyceryl Oleate, Glyceryl Rosinate, Microcrystalline Cellulose, Olea Europaea (Olive) Fruit Oil, Olea Europaea (Olive) Oil Unsaponifiables, Propanediol, Ricinus Communis (Castor) Seed Oil, Water

OTHER SAFETY INFORMATION

Protect this product from excessive heat and direct sun • May stain some fabrics and surfaces

QUESTIONS

212-627-0377 M-F 9am to 5pm EST